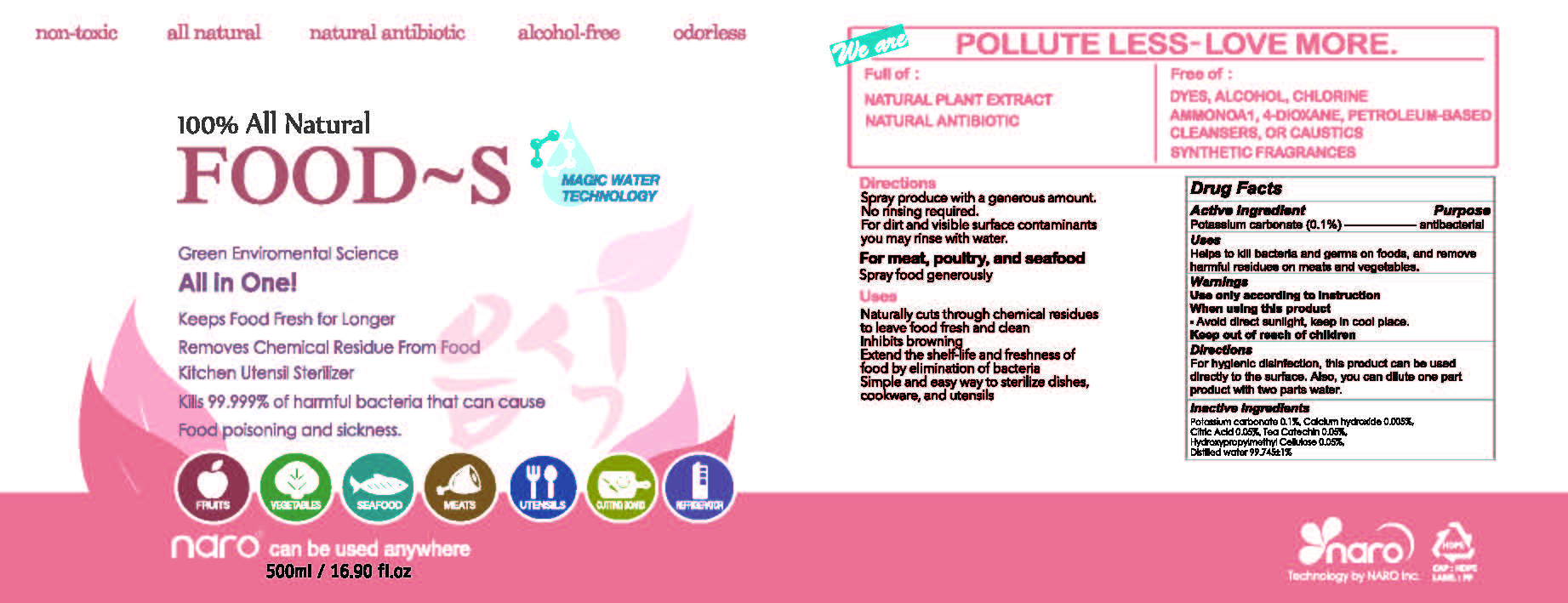 DRUG LABEL: FOOD-S
NDC: 71957-0002 | Form: LIQUID
Manufacturer: NARO, INC.
Category: otc | Type: HUMAN OTC DRUG LABEL
Date: 20180111

ACTIVE INGREDIENTS: POTASSIUM CARBONATE 0.1 g/100 mL
INACTIVE INGREDIENTS: HYPROMELLOSE, UNSPECIFIED; CALCIUM HYDROXIDE

ACTIVE INGREDIENT

Potassium carbonate

INACTIVE INGREDIENT

Calcium hydroxide, Citric acid, Tea catechin, Hydroxypropylmethylcellulose, Distilled water

PURPOSE

Antibacterial

Keep out of reach of children

INDICATIONS AND USAGE

For hygienic disinfection, this product can be used directly to the surface. Also, you can dilute one part product with two parts water.

Warnings
Use only according to instruction
When using this product

- Avoid direct sunlight, keep in cool place.

DOSAGE AND ADMINISTRATION

For external use only